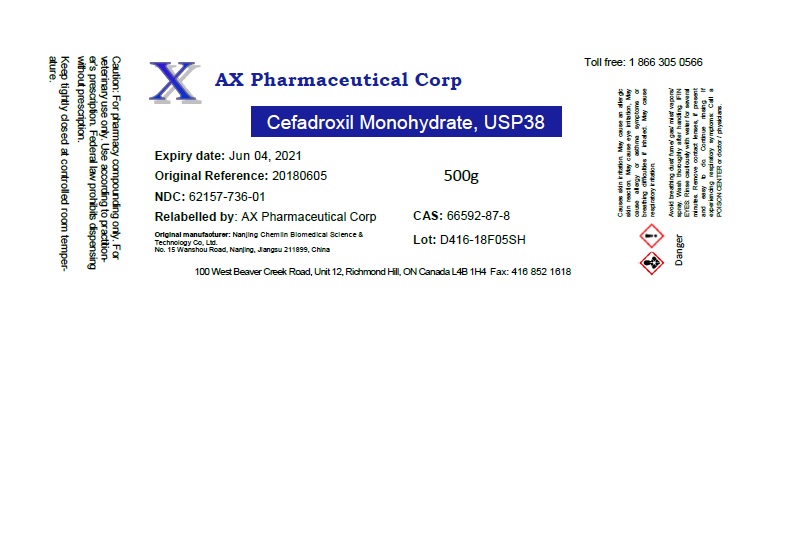 DRUG LABEL: Cefadroxil Monohydrate
NDC: 62157-736 | Form: POWDER
Manufacturer: AX Pharmaceutical Corp
Category: other | Type: BULK INGREDIENT
Date: 20181220

ACTIVE INGREDIENTS: CEFADROXIL 1 g/1 g

Cefadroxil Monohydrate